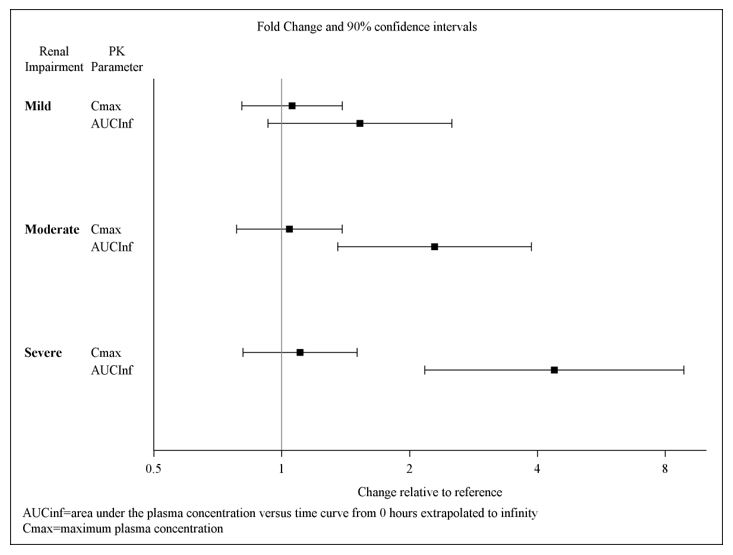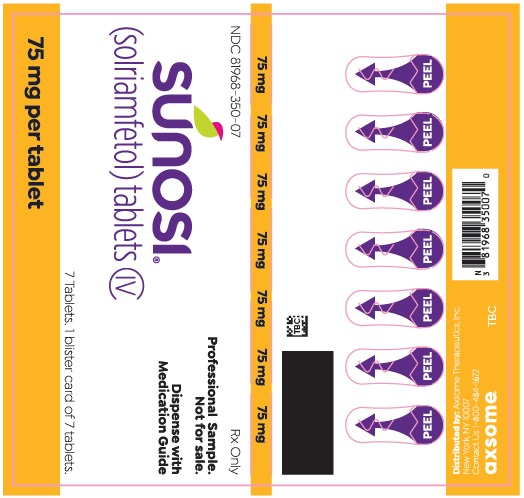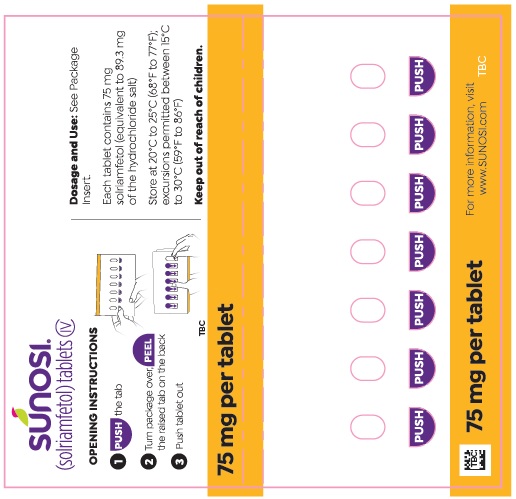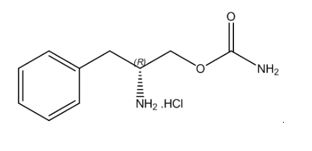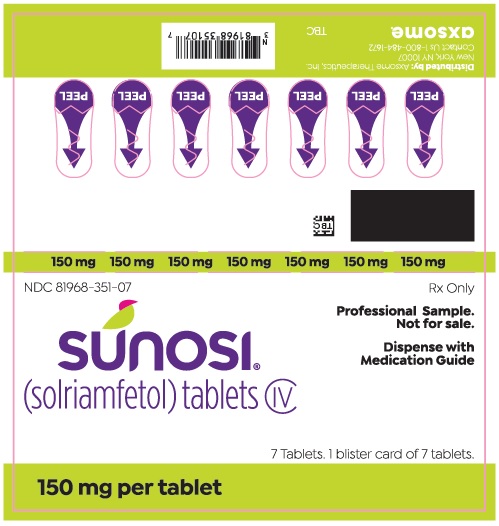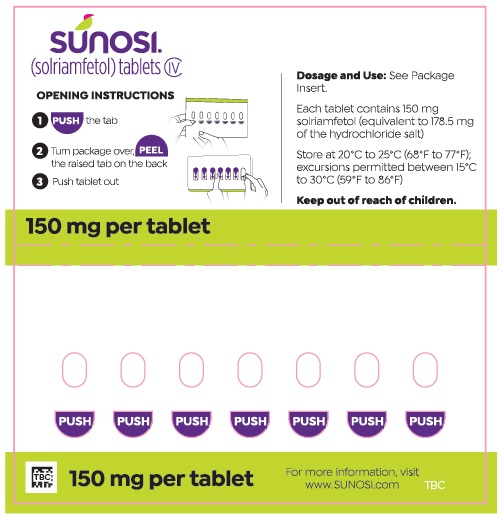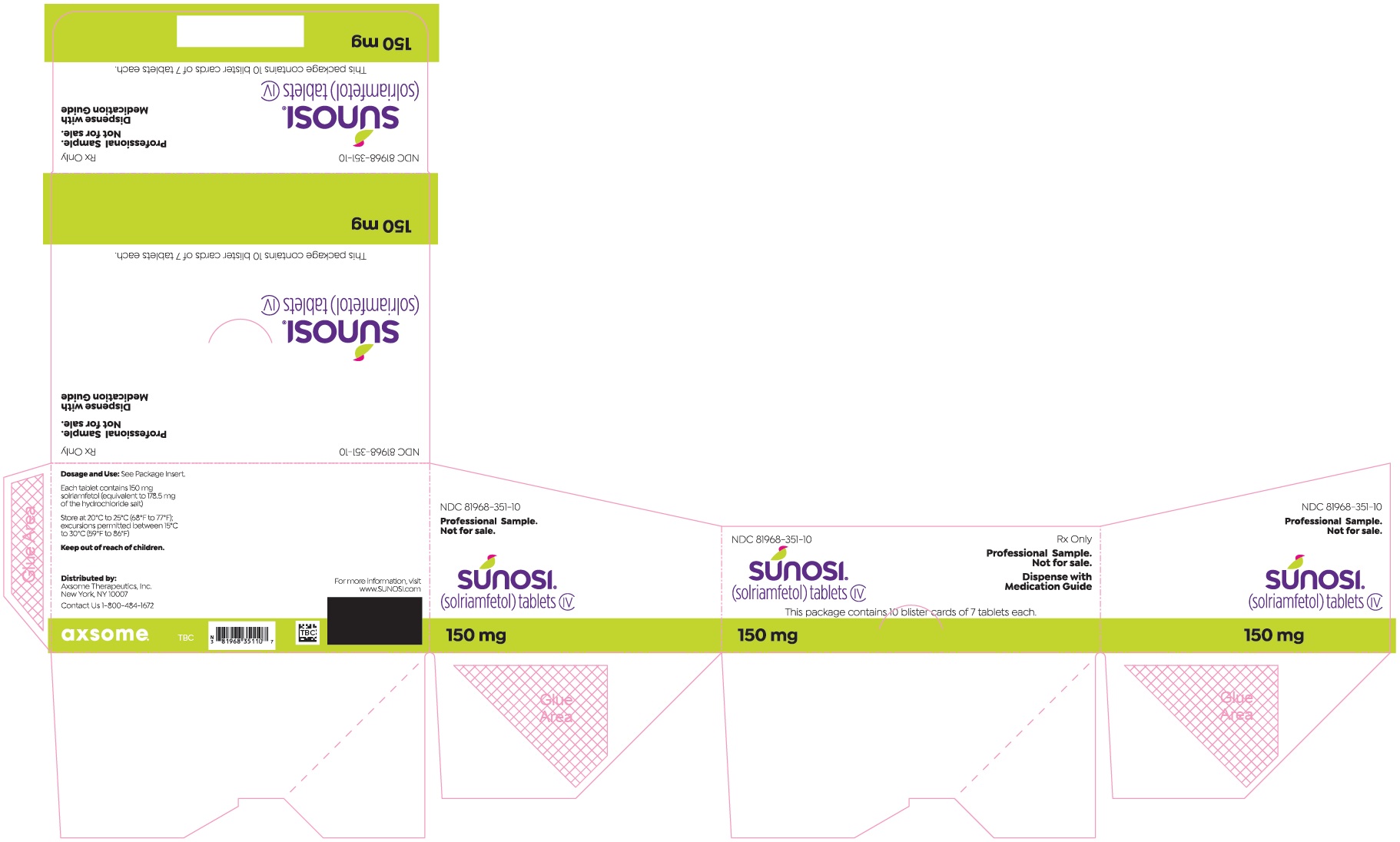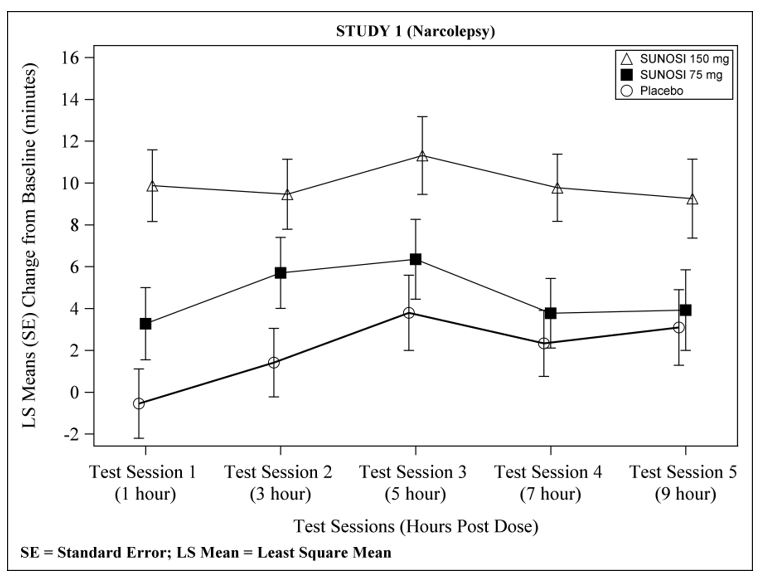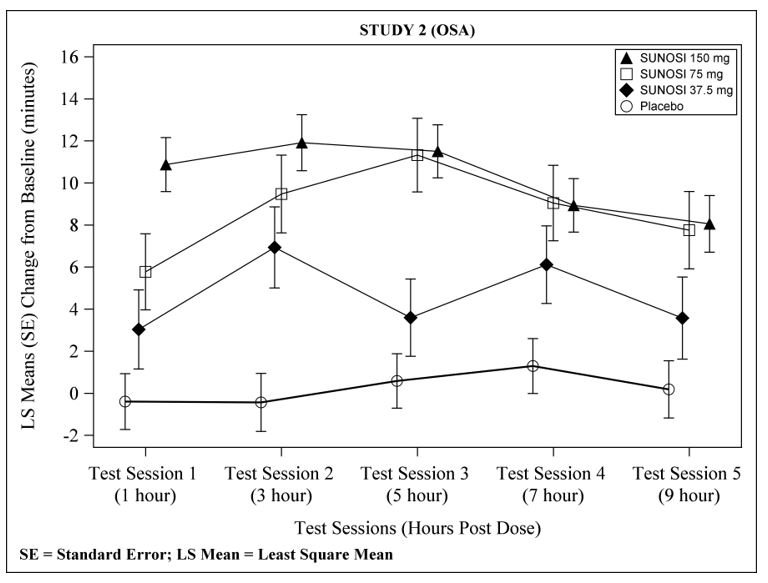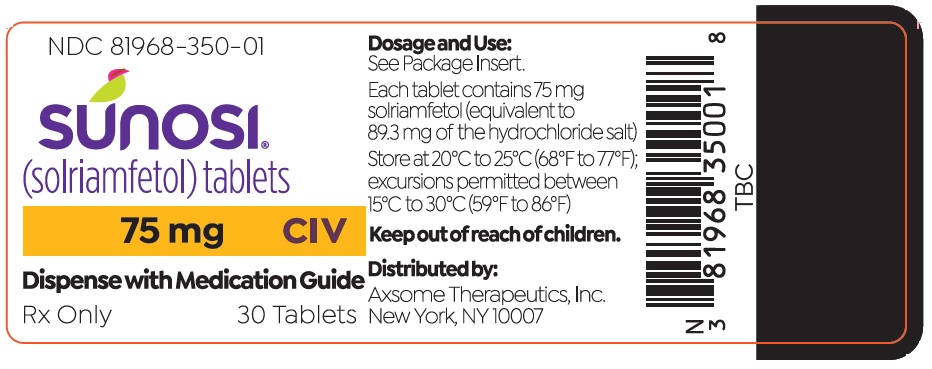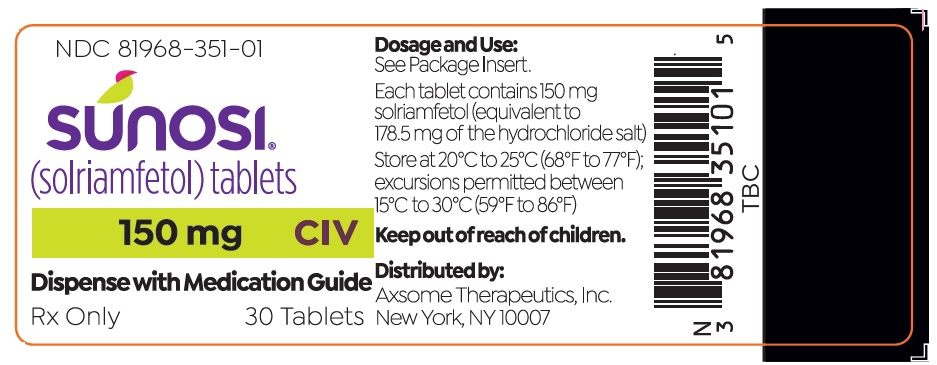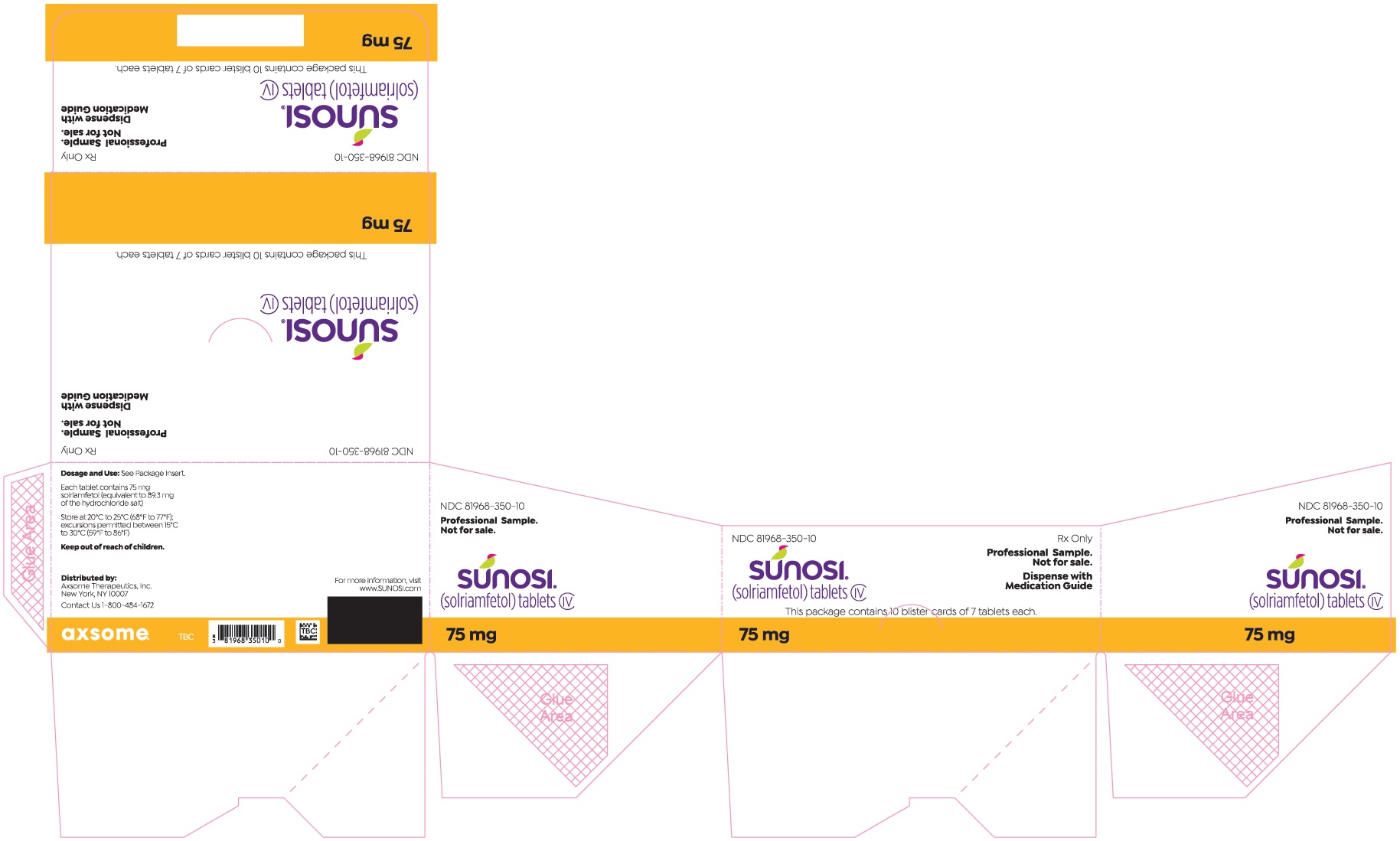 DRUG LABEL: SUNOSI
NDC: 81968-350 | Form: TABLET, FILM COATED
Manufacturer: Axsome Therapeutics, Inc.
Category: prescription | Type: HUMAN PRESCRIPTION DRUG LABEL
Date: 20260113
DEA Schedule: CIV

ACTIVE INGREDIENTS: SOLRIAMFETOL 75 mg/1 1
INACTIVE INGREDIENTS: HYDROXYPROPYL CELLULOSE (90000 WAMW) 2.75 mg/1 1; MAGNESIUM STEARATE 0.5 mg/1 1; POLYVINYL ALCOHOL, UNSPECIFIED 1.3 mg/1 1; POLYETHYLENE GLYCOL 3350 0.65 mg/1 1; TITANIUM DIOXIDE 0.58 mg/1 1; TALC 0.48 mg/1 1; FERRIC OXIDE YELLOW 0.23 mg/1 1

HIGHLIGHTS OF PRESCRIBING INFORMATION

These highlights do not include all the information needed to use SUNOSI safely and effectively. See full prescribing information for SUNOSI.
SUNOSI® (solriamfetol) tablets, for oral use, CIV
Initial U.S. Approval: 2019

1 INDICATIONS AND USAGE

SUNOSI is a dopamine and norepinephrine reuptake inhibitor (DNRI) indicated to improve wakefulness in adult patients with excessive daytime sleepiness associated with narcolepsy or obstructive sleep apnea (OSA). (1)

Limitations of Use

SUNOSI is not indicated to treat the underlying airway obstruction in OSA. Ensure that the underlying airway obstruction is treated (e.g., with continuous positive airway pressure (CPAP)) for at least one month prior to initiating SUNOSI for excessive daytime sleepiness. Modalities to treat the underlying airway obstruction should be continued during treatment with SUNOSI. SUNOSI is not a substitute for these modalities. (1)

2 DOSAGE AND ADMINISTRATION

- Administer once daily upon awakening. Avoid administration within 9 hours of planned bedtime because of the potential to interfere with sleep. (2.2)
- Starting dose for patients with narcolepsy: 75 mg once daily. (2.3)
- Starting dose for patients with OSA: 37.5 mg once daily. (2.4)
- Dose may be increased at intervals of at least 3 days. (2.3, 2.4)
- Maximum dose is 150 mg once daily. (2.3, 2.4)
- Renal impairment (2.5, 8.6, 12.3):
  - Moderate impairment: Starting dose is 37.5 mg once daily.
    - May increase to 75 mg once daily after at least 7 days.
  - Severe impairment: Starting dose and maximum dose is 37.5 mg once daily.
  - End stage renal disease (ESRD): Not recommended.

3 DOSAGE FORMS AND STRENGTHS

Tablets: 75 mg (functionally scored) and 150 mg. (3)

4 CONTRAINDICATIONS

- Concurrent treatment with a monoamine oxidase inhibitor (MAOI) or use of an MAOI within the preceding 14 days. (4)

5 WARNINGS AND PRECAUTIONS

- Blood Pressure and Heart Rate Increases: Measure heart rate and blood pressure prior to initiating and periodically throughout treatment. Control hypertension before and during therapy. Avoid use in patients with unstable cardiovascular disease, serious heart arrhythmias, or other serious heart problems. (5.1)
- Psychiatric Symptoms: Use caution in treating patients with a history of psychosis or bipolar disorders. Consider dose reduction or discontinuation of SUNOSI if psychiatric symptoms develop. (5.2)

6 ADVERSE REACTIONS

Most common adverse reactions (≥ 5% and greater than placebo): headache, nausea, decreased appetite, insomnia, and anxiety. (6.1)

To report SUSPECTED ADVERSE REACTIONS, contact Axsome Therapeutics, Inc. at 1-800-484-1672 or FDA at 1-800-FDA-1088 or www.fda.gov/medwatch.

7 DRUG INTERACTIONS

Drugs that Increase Blood Pressure and/or Heart Rate and Dopaminergic Drugs: Use caution when co-administering with SUNOSI. (7.2, 7.3)

FULL PRESCRIBING INFORMATION

1 INDICATIONS AND USAGE

SUNOSI is indicated to improve wakefulness in adult patients with excessive daytime sleepiness associated with narcolepsy or obstructive sleep apnea (OSA) [see Clinical Studies (14)].

Limitations of Use

SUNOSI is not indicated to treat the underlying airway obstruction in OSA. Ensure that the underlying airway obstruction is treated (e.g., with continuous positive airway pressure (CPAP)) for at least one month prior to initiating SUNOSI for excessive daytime sleepiness. Modalities to treat the underlying airway obstruction should be continued during treatment with SUNOSI. SUNOSI is not a substitute for these modalities.

2 DOSAGE AND ADMINISTRATION

2.1 Important Considerations Prior to Initiating Treatment

Prior to initiating treatment with SUNOSI, ensure blood pressure is adequately controlled [see Warnings and Precautions (5.1)].

2.2 General Administration Instructions

Administer SUNOSI orally upon awakening with or without food. Avoid taking SUNOSI within 9 hours of planned bedtime because of the potential to interfere with sleep if taken too late in the day.

SUNOSI 75 mg tablets are functionally scored tablets that can be split in half (37.5 mg) at the score line.

2.3 Dosage in Narcolepsy

Initiate SUNOSI at 75 mg once daily in adults with narcolepsy. The recommended dose range for SUNOSI is 75 mg to 150 mg once daily. Based on efficacy and tolerability, the dosage of SUNOSI may be doubled at intervals of at least 3 days. The maximum recommended dose is 150 mg once daily. Dosages above 150 mg daily do not confer increased effectiveness sufficient to outweigh dose-related adverse reactions [see Warnings and Precautions (5.1)].

2.4 Dosage in OSA

Initiate SUNOSI at 37.5 mg once daily in adults with OSA. The recommended dosage range for SUNOSI is 37.5 mg to 150 mg once daily. Based on efficacy and tolerability, the dosage of SUNOSI may be doubled at intervals of at least 3 days. The maximum recommended dosage is 150 mg once daily. Dosages above 150 mg daily do not confer increased effectiveness sufficient to outweigh dose-related adverse reactions [see Warnings and Precautions (5.1)].

2.5 Dosage Recommendations in Patients with Renal Impairment

Moderate renal impairment (eGFR 30-59 mL/min/1.73 m^2): Initiate dosing at 37.5 mg once daily. Based on efficacy and tolerability, dose may be increased to a maximum of 75 mg once daily after at least 7 days [see Use in Specific Populations (8.6), Clinical Pharmacology (12.3)].

Severe renal impairment (eGFR 15-29 mL/min/1.73 m^2): Administer 37.5 mg once daily. The maximum recommended daily dose is 37.5 mg [see Use in Specific Populations (8.6), Clinical Pharmacology (12.3)].

End Stage Renal Disease (eGFR <15 mL/min/1.73 m^2): SUNOSI is not recommended for use in patients with ESRD [see Use in Specific Populations (8.6), Clinical Pharmacology (12.3)].

3 DOSAGE FORMS AND STRENGTHS

SUNOSI 75 mg – (75 mg solriamfetol equivalent to 89.3 mg of the hydrochloride salt) dark yellow oblong tablet with "75" debossed on one side and a functional score line on the opposite side.

SUNOSI 150 mg – (150 mg solriamfetol equivalent to 178.5 mg of the hydrochloride salt) yellow oblong tablet with "150" debossed on one side.

4 CONTRAINDICATIONS

SUNOSI is contraindicated in patients receiving concomitant treatment with monoamine oxidase (MAO) inhibitors, or within 14 days following discontinuation of monoamine oxidase inhibitor, because of the risk of hypertensive reaction [see Drug Interactions (7.1)].

5 WARNINGS AND PRECAUTIONS

5.1 Blood Pressure and Heart Rate Increases

SUNOSI increases systolic blood pressure, diastolic blood pressure, and heart rate in a dose-dependent fashion [see Adverse Reactions (6.1)].

Epidemiological data show that chronic elevations in blood pressure increase the risk of major adverse cardiovascular events (MACE), including stroke, heart attack, and cardiovascular death. The magnitude of the increase in absolute risk is dependent on the increase in blood pressure and the underlying risk of MACE in the population being treated. Many patients with narcolepsy and OSA have multiple risk factors for MACE, including hypertension, diabetes, hyperlipidemia, and high body mass index (BMI).

Assess blood pressure and control hypertension before initiating treatment with SUNOSI. Monitor blood pressure regularly during treatment and treat new-onset hypertension and exacerbations of pre-existing hypertension. Exercise caution when treating patients at higher risk of MACE, particularly patients with known cardiovascular and cerebrovascular disease, pre-existing hypertension, and patients with advanced age. Use caution with other drugs that increase blood pressure and heart rate [see Drug Interactions (7.2)].

Periodically reassess the need for continued treatment with SUNOSI. If a patient experiences increases in blood pressure or heart rate that cannot be managed with dose reduction of SUNOSI or other appropriate medical intervention, consider discontinuation of SUNOSI.

Patients with moderate or severe renal impairment may be at a higher risk of increases in blood pressure and heart rate because of the prolonged half-life of SUNOSI [see Dosage and Administration (2.5), Clinical Pharmacology (12.3)].

5.2 Psychiatric Symptoms

Psychiatric adverse reactions have been observed in clinical trials with SUNOSI, including anxiety, insomnia, and irritability [see Adverse Reactions (6.1)].

SUNOSI has not been evaluated in patients with psychosis or bipolar disorders. Exercise caution when treating patients with SUNOSI who have a history of psychosis or bipolar disorders.

Patients with moderate or severe renal impairment may be at a higher risk of psychiatric symptoms because of the prolonged half-life of SUNOSI [see Dosage and Administration (2.5), Clinical Pharmacology (12.3)].

Patients treated with SUNOSI should be observed for the possible emergence or exacerbation of psychiatric symptoms. If psychiatric symptoms develop in association with the administration of SUNOSI, consider dose reduction or discontinuation of SUNOSI.

6 ADVERSE REACTIONS

The following adverse reactions are discussed in greater detail in other sections of the label:

- Blood Pressure and Heart Rate Increases [see Warnings and Precautions (5.1)]
- Psychiatric Symptoms [see Warnings and Precautions (5.2)]

6.1 Clinical Trials Experience

Because clinical trials are conducted under widely varying conditions, adverse reaction rates observed in clinical trials of a drug cannot be directly compared to rates in the clinical trials of another drug and may not reflect the rates observed in practice.

The safety of SUNOSI has been evaluated in 930 patients (ages 18 to 75 years) with narcolepsy or OSA. Among these patients, 396 were treated with SUNOSI in the 12-week placebo-controlled trials at doses of 37.5 mg (OSA only), 75 mg, and 150 mg once daily. Information provided below is based on the pooled 12-week placebo-controlled studies in patients with narcolepsy or OSA.

Most Common Adverse Reactions

The most common adverse reactions (incidence ≥ 5% and greater than placebo) reported more frequently with the use of SUNOSI than placebo in either the narcolepsy or OSA populations were headache, nausea, decreased appetite, anxiety, and insomnia.

Table 1 presents the adverse reactions that occurred at a rate of ≥ 2% and more frequently in SUNOSI-treated patients than in placebo-treated patients in the narcolepsy population.

Table 1: Adverse Reactions ≥ 2% in Patients Treated with SUNOSI and Greater than Placebo in Pooled 12-Week Placebo-Controlled Clinical Trials in Narcolepsy (75 mg and 150 mg)
 | Narcolepsy
System Organ Class | Placebo N = 108 (%) | SUNOSI N = 161 (%)
Metabolism and Nutrition Disorders Decreased appetite | 1 | 9
Psychiatric Disorders Insomnia* Anxiety* | 4 1 | 5 6
Nervous System Disorders Headache* | 7 | 16
Cardiac Disorders Palpitations | 1 | 2
Gastrointestinal Disorders Nausea* Dry mouth Constipation | 4 2 1 | 7 4 3
* “Insomnia” includes insomnia, initial insomnia, middle insomnia, and terminal insomnia. “Anxiety” includes anxiety, nervousness, and panic attack. “Headache” includes headache, tension headache, and head discomfort. “Nausea” includes nausea and vomiting.

Table 2 presents the adverse reactions that occurred at a rate of ≥ 2% and more frequently in SUNOSI-treated patients than in placebo-treated patients in the OSA population.

Table 2: Adverse Reactions ≥ 2% in Patients Treated with SUNOSI and Greater than Placebo in Pooled 12-Week Placebo-Controlled Clinical Trials in OSA (37.5 mg, 75 mg, and 150 mg)
 | OSA
System Organ Class | Placebo N = 118 (%) | SUNOSI N = 235 (%)
Metabolism and Nutrition Disorders Decreased appetite | 1 | 6
Psychiatric Disorders Anxiety* Irritability | 1 0 | 4 3
Nervous System Disorders Dizziness | 1 | 2
Cardiac Disorders Palpitations | 0 | 3
Gastrointestinal Disorders Nausea* Diarrhea Abdominal pain* Dry mouth | 6 1 2 2 | 8 4 3 3
General Disorders and Administration Site Conditions Feeling jittery Chest discomfort | 0 0 | 3 2
Skin and Subcutaneous Tissue Disorders Hyperhidrosis | 0 | 2
* “Anxiety” includes anxiety, nervousness, and panic attack. “Nausea” includes nausea and vomiting. “Abdominal pain” includes abdominal pain, abdominal pain upper, and abdominal discomfort.

Other Adverse Reactions Observed During the Premarketing Evaluation of SUNOSI

Other adverse reactions of < 2% incidence but greater than placebo are shown below. The following list does not include adverse reactions: 1) already listed in previous tables or elsewhere in the labeling, 2) for which a drug cause was remote, 3) which were so general as to be uninformative, or 4) which were not considered to have clinically significant implications.

Narcolepsy population:

Psychiatric disorders: agitation, bruxism, irritability

Respiratory, thoracic and mediastinal disorders: cough

Skin and subcutaneous tissue disorders: hyperhidrosis

General disorders and administration site conditions: feeling jittery, thirst, chest discomfort, chest pain

Investigations: weight decreased

OSA population:

Psychiatric disorders: bruxism, restlessness

Nervous system disorders: disturbance in attention, tremor

Respiratory, thoracic and mediastinal disorders: cough, dyspnea

Gastrointestinal disorders: constipation, vomiting

Investigations: weight decreased

Dose-Dependent Adverse Reactions

In the 12-week placebo-controlled clinical trials that compared doses of 37.5 mg, 75 mg, and 150 mg daily of SUNOSI to placebo, the following adverse reactions were dose-related: headache, nausea, decreased appetite, anxiety, diarrhea, and dry mouth (Table 3).

Table 3: Dose-Dependent Adverse Reactions ≥ 2% in Patients Treated with SUNOSI and Greater than Placebo in Pooled 12-Week Placebo-Controlled Clinical Trials in Narcolepsy and OSA
 | Placebo N = 226 (%) | SUNOSI 37.5 mg N = 58* (%) | SUNOSI 75 mg N = 120 (%) | SUNOSI 150 mg N = 218 (%)
Headache** | 8 | 7 | 9 | 13
Nausea** | 5 | 7 | 5 | 9
Decreased appetite | 1 | 2 | 7 | 8
Anxiety | 1 | 2 | 3 | 7
Dry mouth | 2 | 2 | 3 | 4
Diarrhea | 2 | 2 | 4 | 5
* In OSA only.
** “Headache” includes headache, tension headache, and head discomfort. “Nausea” includes nausea and vomiting.

Adverse Reactions Resulting in Discontinuation of Treatment

In the 12-week placebo-controlled clinical trials, 11 of the 396 patients (3%) who received SUNOSI discontinued because of an adverse reaction compared to 1 of the 226 patients (< 1%) who received placebo. The adverse reactions resulting in discontinuation that occurred in more than one SUNOSI-treated patient and at a higher rate than placebo were: anxiety (2/396; < 1%), palpitations (2/396; < 1%), and restlessness (2/396; < 1%).

Increases in Blood Pressure and Heart Rate

SUNOSI’s effects on blood pressure and heart rate are summarized below. Table 4 shows maximum mean changes in blood pressure and heart rate recorded at sessions where the Maintenance of Wakefulness Test (MWT) was administered [see Clinical Studies (14)]. Table 5 summarizes 24-hour ambulatory blood pressure monitoring (ABPM) and ambulatory heart rate monitoring performed in the outpatient setting.

Table 4: Maximal Mean Changes in Blood Pressure and Heart Rate Assessed at MWT Sessions from Baseline through Week 12: Mean (95% CI)*
 |  | Placebo | SUNOSI 37.5 mg | SUNOSI 75 mg | SUNOSI 150 mg | SUNOSI 300 mg**
Narcolepsy STUDY 1 | n | 52 | - | 51 | 49 | 53
Narcolepsy STUDY 1 | SBP | 3.5 (0.7, 6.4) | - | 3.1 (0.1, 6.0) | 4.9 (1.7, 8.2) | 6.8 (3.2, 10.3)
Narcolepsy STUDY 1 | n | 23 | - | 47 | 49 | 53
Narcolepsy STUDY 1 | DBP | 1.8 (-1.8, 5.5) | - | 2.2 (0.2, 4.1) | 4.2 (2.0, 6.5) | 4.2 (1.5, 6.9)
Narcolepsy STUDY 1 | n | 48 | - | 26 | 49 | 53
Narcolepsy STUDY 1 | HR | 2.3 (-0.1, 4.7) | - | 3.7 (0.4, 6.9) | 4.9 (2.3, 7.6) | 6.5 (3.9, 9.0)
OSA STUDY 2 | n | 35 | 17 | 54 | 103 | 35
OSA STUDY 2 | SBP | 1.7 (-1.4, 4.9) | 4.6 (-1.1, 10.2) | 3.8 (1.2, 6.4) | 2.4 (0.4, 4.4) | 4.5 (1.1, 7.9)
OSA STUDY 2 | n | 99 | 17 | 17 | 107 | 91
OSA STUDY 2 | DBP | 1.4 (-0.1, 2.9) | 1.9 (-2.3, 6.0) | 3.2 (-0.9, 7.3) | 1.8 (0.4, 3.2) | 3.3 (1.8, 4.8)
OSA STUDY 2 | n | 106 | 17 | 51 | 102 | 91
OSA STUDY 2 | HR | 1.7 (0.1, 3.3) | 1.9 (-1.9, 5.7) | 3.3 (0.6, 6.0) | 2.9 (1.4, 4.4) | 4.5 (3.0, 6.0)
SBP = systolic blood pressure; DBP = diastolic blood pressure; HR = heart rate
* For study weeks 1, 4, and 12, SBP, DBP, and HR were assessed pre-dose and every 1-2 hours for 10 hours after test drug administration. For all time points at all visits, the mean change from baseline was calculated, by indication and dose, for all patients with a valid assessment. The table shows, by indication and dose, the mean changes from baseline for the week and time point with the maximal change in SBP, DBP, and HR.
** The maximum recommended daily dose is 150 mg. Dosages above 150 mg daily do not confer increased effectiveness sufficient to outweigh dose-related adverse reactions.

Table 5: Blood Pressure and Heart Rate by 24-hour Ambulatory Monitoring: Mean Change (95% CI) from Baseline at Week 8
 |  | Placebo | SUNOSI 37.5 mg | SUNOSI 75 mg | SUNOSI 150 mg | SUNOSI 300 mg**
Narcolepsy STUDY 1 | n* | 46 |  | 44 | 44 | 40
Narcolepsy STUDY 1 | SBP | -0.4 (-3.1, 2.4) | - | 1.6 (-0.4, 3.5) | -0.5 (-2.1, 1.1) | 2.4 (0.5, 4.3)
Narcolepsy STUDY 1 | DBP | -0.2 (-1.9, 1.6) | - | 1.0 (-0.4, 2.5) | 0.8 (-0.4, 2.0) | 3.0 (1.4, 4.5)
Narcolepsy STUDY 1 | HR | 0.0 (-1.9, 2.0) | - | 0.2 (-2.1, 2.4) | 1.0 (-1.2, 3.2) | 4.8 (2.3, 7.2)
OSA STUDY 2 | n* | 92 | 43 | 49 | 96 | 84
OSA STUDY 2 | SBP | -0.2 (-1.8, 1.4) | 1.8 (-1.1, 4.6) | 2.6 (0.02, 5.3) | -0.2 (-2.0, 1.6) | 2.8 (-0.1, 5.8)
OSA STUDY 2 | DBP | 0.2 (-0.9, 1.3) | 1.4 (-0.4, 3.2) | 1.5 (-0.04, 3.1) | -0.1 (-1.1, 1.0) | 2.4 (0.5, 4.4)
OSA STUDY 2 | HR | -0.4 (-1.7, 0.9) | 0.4 (-1.4, 2.2) | 1.0 (-0.9, 2.81) | 1.7 (0.5, 2.9) | 1.6 (0.3, 2.9)
SBP = systolic blood pressure; DBP = diastolic blood pressure; HR = heart rate
* Number of patients who had at least 50% valid ABPM readings.
** The maximum recommended daily dose is 150 mg. Dosages above 150 mg daily do not confer increased effectiveness sufficient to outweigh dose-related adverse reactions.

6.2 Postmarketing Experience

The following adverse reactions have been reported during post-approval use of SUNOSI. Because these reactions are reported voluntarily from a population of uncertain size, it is not always possible to reliably estimate their frequency or establish a causal relationship to drug exposure:

Immune system disorders: Hypersensitivity (rash erythematous, rash [unspecified], and urticaria).

7 DRUG INTERACTIONS

7.1 Monoamine Oxidase (MAO) Inhibitors

Do not administer SUNOSI concomitantly with MAOIs or within 14 days after discontinuing MAOI treatment. Concomitant use of MAO inhibitors and noradrenergic drugs may increase the risk of a hypertensive reaction. Potential outcomes include death, stroke, myocardial infarction, aortic dissection, ophthalmological complications, eclampsia, pulmonary edema, and renal failure [see Contraindications (4)].

7.2 Drugs that Increase Blood Pressure and/or Heart Rate

Concomitant use of SUNOSI with other drugs that increase blood pressure and/or heart rate has not been evaluated, and such combinations should be used with caution [see Warnings and Precautions (5.1)].

7.3 Dopaminergic Drugs

Dopaminergic drugs that increase levels of dopamine or that bind directly to dopamine receptors might result in pharmacodynamic interactions with SUNOSI. Interactions with dopaminergic drugs have not been evaluated with SUNOSI. Use caution when concomitantly administering dopaminergic drugs with SUNOSI.

8 USE IN SPECIFIC POPULATIONS

8.1 Pregnancy

Pregnancy Exposure Registry

There is a pregnancy exposure registry that monitors pregnancy outcomes in women exposed to SUNOSI during pregnancy. Healthcare providers are encouraged to register pregnant patients, or pregnant women may enroll themselves in the registry by calling 1-877-283-6220 or contacting the company at www.SunosiPregnancyRegistry.com.

Risk Summary

Available data from case reports are not sufficient to determine drug-associated risks of major birth defects, miscarriage, or adverse maternal or fetal outcomes. In animal reproductive studies, oral administration of solriamfetol during organogenesis caused maternal and fetal toxicities in rats and rabbits at doses ≥ 4 and 5 times and was teratogenic at doses 19 and ≥ 5 times, respectively, the maximum recommended human dose (MRHD) of 150 mg based on mg/m^2 body surface area. Oral administration of solriamfetol to pregnant rats during pregnancy and lactation at doses ≥ 7 times the MRHD based on mg/m^2 body surface area resulted in maternal toxicity and adverse effects on fertility, growth, and development in offspring (see Data).

The estimated background risk of major birth defects and miscarriage for the indicated population is unknown. All pregnancies have a background risk of birth defect, loss, or other adverse outcomes. In the U.S. general population, the estimated background risks of major birth defects and miscarriage in clinically recognized pregnancies are 2% to 4% and 15% to 20%, respectively.

Data

Animal Data

Solriamfetol was administered orally to pregnant rats during the period of organogenesis at 15, 67, and 295 mg/kg/day, which are approximately 1, 4, and 19 times the MRHD based on mg/m^2 body surface area. Solriamfetol at ≥ 4 times the MRHD caused maternal toxicity that included hyperactivity, significant decreases in body weight, weight gain, and food consumption. Fetal toxicity at these maternally toxic doses included increased incidence of early resorption and post-implantation loss, and decreased fetal weight. Solriamfetol was teratogenic at 19 times the MRHD; it increased the incidence of fetal malformations that included severe sternebrae mal-alignment, hindlimb rotation, bent limb bones, and situs inversus. This dose was also maternally toxic. The no-adverse-effect level for malformation is 4 times and for maternal and embryofetal toxicity is approximately 1 times the MRHD based on mg/m^2 body surface area.

Solriamfetol was administered orally to pregnant rabbits during the period of organogenesis at 17, 38, and 76 mg/kg/day, which are approximately 2, 5, and 10 times the MRHD based on mg/m^2 body surface area. Solriamfetol at 10 times the MRHD caused maternal toxicity of body weight loss and decreased food consumption. Solriamfetol was teratogenic at ≥ 5 times the MRHD, it caused fetal skeletal malformation (slight-to-moderate sternebrae mal-alignment) and decreased fetal weight. The no-adverse-effect level for malformation and fetal toxicity is approximately 2 times and for maternal toxicity is approximately 5 times the MRHD based on mg/m^2 body surface area.

Solriamfetol was administered orally to pregnant rats during the period of organogenesis from gestation day 7 through lactation day 20 post-partum, at 35, 110, and 350 mg/kg/day, which are approximately 2, 7, and 22 times the MRHD based on mg/m^2 body surface area. At ≥ 7 times the MRHD, solriamfetol caused maternal toxicity that included decreased body weight gain, decreased food consumption, and hyperpnea. At these maternally toxic doses, fetal toxicity included increased incidence of stillbirth, postnatal pup mortality, and decreased pup weight. Developmental toxicity in offspring after lactation day 20 included decreased body weight, decreased weight gain, and delayed sexual maturation. Mating and fertility of offspring were decreased at maternal doses 22 times the MRHD without affecting learning and memory. The no-adverse-effect level for maternal and developmental toxicity is approximately 2 times the MRHD based on mg/m^2 body surface area.

8.2 Lactation

Risk Summary

Available data from a lactation study in 6 women indicate that solriamfetol is present in human milk. The daily infant dose is 0.112 mg/kg (based on nominal infant weight of 6 kg) and the relative infant dose (RID) is approximately 5.5% of the maternal weight-adjusted dosage (see Data). Data are insufficient to determine effects of solriamfetol on a breastfed infant or its effects on milk production.

The developmental and health benefits of breastfeeding should be considered along with the mother’s clinical need for SUNOSI and any potential adverse effects on the breastfed infant from SUNOSI or from the underlying maternal condition.

Clinical Considerations

Monitor infants exposed to SUNOSI for signs of agitation, insomnia, and reduced weight gain.

Data

A single-dose milk and plasma lactation study was conducted in 6 healthy adult lactating women who were between 10 days and 52 weeks postpartum and were administered a single oral 150 mg dose of SUNOSI. The cumulative median amount excreted in breast milk was 0.67 mg over 72 hours, which is about 5.5% of the maternal dose on a weight-adjusted basis. Of the total amount of solriamfetol excreted in breast milk over 72 hours, approximately 78% and 98% were excreted by 8 and 24 hours, respectively, with an apparent mean elimination half-life in breast milk of about 5 hours.

8.4 Pediatric Use

Safety and effectiveness in pediatric patients have not been established. Clinical studies of SUNOSI in pediatric patients have not been conducted.

8.5 Geriatric Use

Of the total number of patients in the narcolepsy and OSA clinical studies treated with SUNOSI, 13% (123/930) were 65 years of age or over.

No clinically meaningful differences in safety or effectiveness were observed between elderly and younger patients.

Solriamfetol is predominantly eliminated by the kidney. Because elderly patients are more likely to have decreased renal function, dosing may need to be adjusted based on eGFR in these patients. Consideration should be given to the use of lower doses and close monitoring in this population [see Dosage and Administration (2.5)].

8.6 Renal Impairment

Dosage adjustment is not required for patients with mild renal impairment (eGFR 60-89 mL/min/1.73 m^2). Dosage adjustment is recommended for patients with moderate to severe renal impairment (eGFR 15-59 mL/min/1.73 m^2). SUNOSI is not recommended for patients with end stage renal disease (eGFR <15 mL/min/1.73 m^2) [see Dosage and Administration (2.5), Warnings and Precautions (5.1, 5.2), Clinical Pharmacology (12.3)].

9 DRUG ABUSE AND DEPENDENCE

9.1 Controlled Substance

SUNOSI contains solriamfetol, a Schedule IV controlled substance.

9.2 Abuse

SUNOSI has potential for abuse. Abuse is the intentional non-therapeutic use of a drug, even once, to achieve a desired psychological or physiological effect. The abuse potential of SUNOSI 300 mg, 600 mg, and 1200 mg (two, four, and eight times the maximum recommended dose, respectively) was assessed relative to phentermine, 45 mg and 90 mg, (a Schedule IV controlled substance) in a human abuse potential study in individuals experienced with the recreational use of stimulants. Results from this clinical study demonstrated that SUNOSI produced Drug Liking scores similar to or lower than phentermine. In this crossover study, elevated mood was reported by 2.4% of placebo-treated subjects, 8 to 24% of SUNOSI-treated subjects, and 10 to 18% of phentermine-treated subjects. A ‘feeling of relaxation’ was reported in 5% of placebo-treated subjects, 5 to 19% of SUNOSI-treated subjects and 15 to 20% of phentermine-treated subjects.

Physicians should carefully evaluate patients for a recent history of drug abuse, especially those with a history of stimulant (e.g., methylphenidate, amphetamine, or cocaine) or alcohol abuse, and follow such patients closely, observing them for signs of misuse or abuse of SUNOSI (e.g., incrementation of doses, drug-seeking behavior).

9.3 Dependence

In a long-term safety and maintenance of efficacy study, the effects of abrupt discontinuation of SUNOSI were evaluated following at least 6 months of SUNOSI use in patients with narcolepsy or OSA. The effects of abrupt discontinuation of SUNOSI were also evaluated during the two-week safety follow-up periods in the Phase 3 studies. There was no evidence that abrupt discontinuation of SUNOSI resulted in a consistent pattern of adverse events in individual subjects that was suggestive of physical dependence or withdrawal.

10 OVERDOSAGE

A specific reversal agent for SUNOSI is not available. Hemodialysis removed approximately 21% of a 75 mg dose in end stage renal disease patients. Overdoses should be managed with primarily supportive care, including cardiovascular monitoring.

Consult with a Certified Poison Control Center at 1-800-222-1222 for latest recommendations.

11 DESCRIPTION

SUNOSI contains solriamfetol, a dopamine and norepinephrine reuptake inhibitor (DNRI). Solriamfetol is a phenylalanine derivative with the systematic name (R)-2-amino-3-phenylpropylcarbamate hydrochloride.

The molecular formula is C10H15N2O2Cl, and the molecular weight is 230.69.

The chemical structure is:

Solriamfetol hydrochloride is a white to off-white solid that is freely soluble in water.

SUNOSI tablets are intended for oral administration. Each 75 mg SUNOSI film-coated tablet contains 75 mg solriamfetol (equivalent to 89.3 mg solriamfetol hydrochloride). Each 150 mg SUNOSI film-coated tablet contains 150 mg solriamfetol (equivalent to 178.5 mg solriamfetol hydrochloride). The inactive ingredients are hydroxypropyl cellulose and magnesium stearate. In addition, the film coating contains: iron oxide yellow, polyethylene glycol, polyvinyl alcohol, talc, and titanium dioxide.

12 CLINICAL PHARMACOLOGY

12.1 Mechanism of Action

The mechanism of action of solriamfetol to improve wakefulness in patients with excessive daytime sleepiness associated with narcolepsy or obstructive sleep apnea is unclear. However, its efficacy could be mediated through its activity as a dopamine and norepinephrine reuptake inhibitor (DNRI).

12.2 Pharmacodynamics

Solriamfetol binds to the dopamine transporter and norepinephrine transporter with low affinity (Ki=14.2 µM and 3.7 µM, respectively), and inhibits the reuptake of dopamine and norepinephrine with low potency (IC50 =2.9 μM and 4.4 μM, respectively). Solriamfetol has no appreciable binding affinity for the serotonin transporter (Ki=81.5 µM) and does not inhibit serotonin reuptake (IC50> 100 μM). Solriamfetol has no appreciable binding affinity to dopamine, serotonin, norepinephrine, GABA, adenosine, histamine, orexin, benzodiazepine, muscarinic acetylcholine, or nicotinic acetylcholine receptors.

Cardiac Electrophysiology

The effect of solriamfetol 300 mg and 900 mg (twice and six times the maximum recommended dose, respectively) on the QTc interval was evaluated in a randomized, double-blind, placebo-, and positive-controlled (moxifloxacin 400 mg), 4-period, crossover study in 60 healthy subjects. A large increase in heart rate was observed in both solriamfetol treatment groups (mean change from baseline in HR of 21 and 27 bpm in the 300 and 900 mg groups, respectively, compared with 8 bpm in the placebo group). These heart rate effects impact the interpretability of the QTc effects, particularly in the 900 mg group. In this study, solriamfetol 300 mg did not prolong the QTcF interval to a clinically relevant extent.

12.3 Pharmacokinetics

Solriamfetol exhibits linear kinetics over the dose range of 42 to 1008 mg (approximately 0.28 to 6.7 times the maximum recommended dosage). Steady state is reached in 3 days, and once‑daily administration is expected to result in minimal accumulation (1.06 times single‑dose exposure).

Absorption

The oral bioavailability of solriamfetol is approximately 95%. Peak plasma concentration of solriamfetol occurs at a median Tmax of 2 hours (range 1.25 to 3.0 hours) post-dose under fasted conditions.

Effect of Food

Ingestion of solriamfetol with a high-fat meal resulted in minimal change in Cmax and AUCinf; however, a delay of approximately 1 hour in Tmax was observed.

Distribution

The apparent volume of distribution of solriamfetol is approximately 199 L. Plasma protein binding ranged from 13.3% to 19.4% over solriamfetol concentration range of 0.059 to 10.1 mcg/mL in human plasma. The mean blood‑to‑plasma concentration ratio ranged from 1.16 to 1.29.

Elimination

Solriamfetol exhibits first‑order elimination after oral administration. The apparent mean elimination half‑life is about 7.1 hours.

Metabolism

Solriamfetol is minimally metabolized in humans.

Excretion

Approximately 95% of the dose was recovered in urine as unchanged solriamfetol, and 1% or less of the dose was recovered as the minor inactive metabolite N‑acetyl solriamfetol in a mass balance study. Renal clearance (18.2 L/h) represented the majority of apparent total clearance (19.5 L/h). Active tubular secretion is likely involved in the renal elimination of the parent drug.

Specific Populations

Population PK analysis indicated that age, gender, and race do not have clinically relevant effects on the pharmacokinetics of solriamfetol. No dose adjustments were made in clinical studies that enrolled patients ages 65 and above.

Patients with Renal Impairment

Exposures to solriamfetol in patients with renal impairment compared to subjects with normal renal function (eGFR ≥ 90 mL/min/1.73 m^2) are summarized in Figure 1. The half‑life of solriamfetol was increased approximately 1.2‑, 1.9‑, and 3.9‑fold in patients with mild (eGFR 60‑89 mL/min/1.73 m^2), moderate (eGFR 30–59 mL/min/1.73 m^2), or severe (eGFR <30 mL/min/1.73 m^2) renal impairment, respectively. Exposure (AUC) and half-life of solriamfetol was significantly increased in patients with ESRD (eGFR <15 mL/min/1.73 m^2) [see Use in Specific Populations (8.6)]. An average of 21% of solriamfetol was removed by hemodialysis. In general, median Tmax values were not affected by renal impairment.

Figure 1: Effect of Renal Impairment on Solriamfetol Pharmacokinetics

Drug Interaction Studies

In Vitro Studies

CYP and UGT Enzymes: Solriamfetol was minimally metabolized in vitro. Solriamfetol is not an inhibitor of CYPs 1A2, 2A6, 2B6, 2C8, 2C9, 2C19, 2D6, 2E1, or 3A4. It does not induce CYP1A2, 2B6, 3A4, or UGT1A1 enzymes at clinically relevant concentrations.

Transporter Systems: Solriamfetol is a low-avidity substrate of OCT2, MATE1, OCTN1, and OCTN2. Solriamfetol is a weak inhibitor of OCT2 (IC50 of 146 μM) and MATE1 (IC50 of 211 μM), and is not an inhibitor of OCT1, MATE2-K, OCTN1, or OCTN2. Solriamfetol does not appear to be a substrate or inhibitor of P-gp, BCRP, OATP1B1, OATP1B3, OAT1, or OAT3.

Based on in vitro data, clinically significant PK drug interactions with major CYPs and transporters are not expected in patients taking SUNOSI.

13 NONCLINICAL TOXICOLOGY

13.1 Carcinogenesis, Mutagenesis, Impairment of Fertility

Carcinogenesis

Solriamfetol did not increase the incidence of tumors in rats or mice treated orally for up to 101 and 104 weeks at 35, 80, and 200 mg/kg/day (rat), and 20, 65, and 200 mg/kg/day (mouse), respectively. These doses are approximately 2, 6, and 18 times (rat), and 0.4, 2.6, and 7 times (mouse) the MRHD based on AUC.

Mutagenesis

Solriamfetol was not mutagenic in the in vitro bacterial reverse mutation (Ames) assay or clastogenic in the in vitro mammalian chromosomal aberration assay or in the in vivo mouse bone marrow micronucleus assay.

Impairment of Fertility

Solriamfetol did not affect fertility or sperm parameters when administered orally to male rats for 8 weeks at doses of 35 and 110 mg/kg/day, which are approximately 2 and 7 times the MRHD, based on mg/m^2 body surface area. At 350 mg/kg/day, which is approximately 22 times the MRHD based on mg/m^2 body surface area, solriamfetol decreased sperm count and sperm concentration without affecting fertility.

Solriamfetol did not affect fertility when administered orally to female rats for 2 weeks premating, during mating, and through gestation day 7 at 15, 67, and 295 mg/kg/day, which are approximately 1, 4, and 19 times the MRHD, based on mg/m^2 body surface area.

14 CLINICAL STUDIES

14.1 Narcolepsy

The efficacy of SUNOSI in improving wakefulness and reducing excessive daytime sleepiness was demonstrated in a 12-week, multi-center, randomized, double-blind, placebo-controlled, parallel-group study (Study 1; NCT02348593) in adult patients with a diagnosis of narcolepsy according to the ICSD-3 or DSM-5 criteria.

Wakefulness and sleepiness were assessed using the Maintenance of Wakefulness Test (MWT) and the Epworth Sleepiness Scale (ESS). The MWT measures an individual’s ability to remain awake during the daytime in a darkened, quiet environment. Patients were instructed to remain awake for as long as possible during 40-minute test sessions, and sleep latency was determined as the mean number of minutes patients could remain awake in the first four test sessions. The ESS is an 8-item questionnaire by which patients rate their perceived likelihood of falling asleep during usual daily life activities. Change in overall symptom severity was assessed using the Patient Global Impression of Change (PGIc) scale. The PGIc is a 7-point patient-reported scale by which patients rate their symptom change since the beginning of the study. Responses range from “very much improved” to “very much worse.” The co-primary efficacy endpoints were change from baseline in MWT and ESS at Week 12. A pre-specified secondary endpoint was percentage of subjects reported as improved (minimally, much, or very much) at Week 12 by PGIc.

A total of 239 patients with narcolepsy were randomized to receive SUNOSI 75 mg, 150 mg, or 300 mg (two times the maximum recommended daily dose), or placebo once daily. Patients randomized to the 150-mg dose received 75 mg for the first 3 days before increasing to 150 mg.

Demographic and baseline disease characteristics were similar for the SUNOSI and placebo groups. Median age was 34 years (range 18 to 70 years), 65% were female, 80% were Caucasian, 14% were African American, and 3% were Asian. Approximately 51% of patients had cataplexy.

Compared to the placebo group, patients randomized to 150 mg SUNOSI showed statistically significant improvements on the MWT (treatment effect difference: 7.7 minutes, Table 6) and on the ESS (treatment effect difference: 3.8 points, Table 7) at Week 12. These effects were apparent at Week 1 and consistent with the results at Week 12. The change on percentage of subjects reported as improved by PGIc was also statistically significant compared with placebo. There were trends toward improvement in the SUNOSI 75-mg treatment group (Tables 6 and 7); however, these changes were not statistically significant. There was no evidence of differential efficacy in patients with cataplexy and patients without cataplexy. Examination of subgroups by age, race, and sex did not suggest differences in response.

At Week 12, 150 mg of SUNOSI demonstrated improvements in wakefulness compared to placebo as assessed in test sessions 1 (approximately 1 hour post-dose) through 5 (approximately 9 hours post-dose) of the MWT (Figure 2). Nighttime sleep as measured with polysomnography was not affected by the use of SUNOSI in Study 1.

Figure 2: Maintenance of Wakefulness Test Improvements in Test Sessions 1 through 5 in Patients with Narcolepsy in Study 1 at Week 12

14.2 Obstructive Sleep Apnea (OSA)

The efficacy of SUNOSI in improving wakefulness and reducing excessive daytime sleepiness in patients with OSA was demonstrated in a 12-week multi-center, randomized, double-blind, placebo-controlled study (Study 2; NCT02348606) in adults diagnosed with OSA according to ICSD-3 criteria. The co-primary efficacy endpoints were change from baseline in MWT and ESS at Week 12; a pre-specified secondary endpoint was percentage of subjects reported as improved (minimally, much, or very much) at Week 12 by PGIc.

A total of 476 patients with OSA were randomized to receive SUNOSI 37.5 mg, 75 mg, 150 mg, or 300 mg (two times the maximum recommended daily dose), or placebo once daily. Patients randomized to the 150-mg dose received 75 mg for the first 3 days before increasing to 150 mg.

Demographic and baseline disease characteristics were similar for the SUNOSI and placebo groups. Median age was 55 years (range 20 to 75 years), 37% were female, 76% were Caucasian, 19% were African American, and 4% were Asian.

Compared to the placebo group, patients randomized to 37.5 mg, 75 mg, and 150 mg SUNOSI showed statistically significant improvements on the MWT (treatment effect difference: 4.5 minutes, 8.9 minutes, and 10.7 minutes respectively; Table 6) and ESS (treatment effect difference: 1.9 points, 1.7 points, and 4.5 points respectively; Table 7) at Week 12. These effects were apparent at Week 1 and consistent with the results at Week 12. The change on percentage of subjects reported as improved by PGIc was also statistically significant compared with placebo at the 75 mg and 150 mg doses. Examination of subgroups by age, race, and sex did not suggest differences in response.

At Week 12, 37.5 mg, 75 mg, and 150 mg of SUNOSI all demonstrated improvements in wakefulness compared to placebo as assessed in test sessions 1 (approximately 1 hour post-dose) through 5 (approximately 9 hours post-dose) of the MWT (Figure 3). Nighttime sleep as measured with polysomnography was not affected by the use of SUNOSI in Study 2. Patients’ compliance with a primary OSA therapy device was similar across the placebo and SUNOSI treatment groups at baseline, and did not change during the 12-week study period in any treatment group.

Figure 3: Maintenance of Wakefulness Test Improvements in Test Sessions 1 through 5 in Patients with OSA in Study 2 at Week 12

Table 6: Efficacy Results for Maintenance of Wakefulness Test (minutes) in Patients with Narcolepsy (Study 1) and OSA (Study 2)
Indication/ Study | Treatment Group (N) | Baseline Mean (SD) | LS Mean Change from Baseline at Week 12 (SE) | Difference from Placebo (95% CI)
Narcolepsy STUDY 1 | Placebo (58) | 6.2 (5.7) | 2.1 (1.3) | -
Narcolepsy STUDY 1 | SUNOSI 75 mg (59) | 7.5 (5.4) | 4.7 (1.3) | 2.6 (-1.0, 6.3)
Narcolepsy STUDY 1 | SUNOSI 150 mg* (55) | 7.9 (5.7) | 9.8 (1.3) | 7.7 (4.0, 11.3)
OSA STUDY 2 | Placebo (114) | 12.6 (7.1) | 0.2 (1.0) | -
OSA STUDY 2 | SUNOSI 37.5 mg* (56) | 13.6 (8.1) | 4.7 (1.4) | 4.5 (1.2, 7.9)
OSA STUDY 2 | SUNOSI 75 mg* (58) | 12.4 (6.9) | 9.1 (1.4) | 8.9 (5.6, 12.4)
OSA STUDY 2 | SUNOSI 150 mg* (116) | 12.5 (7.2) | 11.0 (1.0) | 10.7 (8.1, 13.4)
SD = standard deviation; SE = standard error; LS Mean = least square mean; CI = confidence interval
Maximum possible MWT score is 40 minutes. A positive change represents improvement.
Difference from Placebo = LS Mean Difference between change from baseline between active drug and placebo.
* Dose that was statistically significantly superior to placebo after adjusting for multiplicity.

Table 7: Efficacy Results for Epworth Sleepiness Scale in Patients with Narcolepsy (Study 1) and OSA (Study 2)
Indication/ Study | Treatment Groups (N) | Baseline Score Mean (SD) | LS Mean Change from Baseline at Week 12 (SE) | Difference from Placebo (95% CI)
Narcolepsy STUDY 1 | Placebo (58) | 17.3 (2.9) | -1.6 (0.7) | -
Narcolepsy STUDY 1 | SUNOSI 75 mg (59) | 17.3 (3.5) | -3.8 (0.7) | -2.2 (-4.0, -0.3)
Narcolepsy STUDY 1 | SUNOSI 150 mg* (55) | 17.0 (3.6) | -5.4 (0.7) | -3.8 (-5.6, -2.0)
OSA STUDY 2 | Placebo (114) | 15.6 (3.3) | -3.3 (0.5) | -
OSA STUDY 2 | SUNOSI 37.5 mg* (56) | 15.1 (3.5) | -5.1 (0.6) | -1.9 (-3.4, -0.3)
OSA STUDY 2 | SUNOSI 75 mg* (58) | 15.0 (3.5) | -5.0 (0.6) | -1.7 (-3.2, -0.2)
OSA STUDY 2 | SUNOSI 150 mg* (116) | 15.1 (3.4) | -7.7 (0.4) | -4.5 (-5.7, -3.2)
SD = standard deviation; SE = standard error; LS Mean = least square mean; CI = confidence interval
Scores range from 0 to 24 with higher scores indicating more severe sleepiness. A negative change represents improvement.
Difference from placebo = LS mean difference between change from baseline between SUNOSI and placebo.
* Dose that was statistically significantly superior to placebo after adjusting for multiplicity.

14.3 Maintenance of Efficacy in Narcolepsy and OSA

The maintenance of effect of SUNOSI in improving wakefulness and reducing excessive daytime sleepiness in patients with narcolepsy and OSA was assessed in two randomized-withdrawal, placebo-controlled studies, Study 3 (NCT02348619) and Study 4 (NCT02348632).) and Study 4 (NCT02348632).

Study 3 was a 6-week, multi-center, double-blind, placebo-controlled, randomized-withdrawal study in 174 adult patients with a diagnosis of OSA. The co-primary efficacy endpoints were change from the beginning to the end of the randomized withdrawal period in MWT and ESS. During a 2-week, open-label titration phase, patients were started on SUNOSI 75 mg once daily, and were titrated to the maximum tolerable dose between 75 mg and 300 mg per day (two times the maximum recommended daily dose). Patients were continued on this dose for a 2-week stable-dose phase. At the end of the stable-dose phase, 124 patients who reported “much” or “very much” improvement on the PGIc and who showed improvements on the MWT and ESS entered a double-blind withdrawal phase and were randomized 1:1 to either continue SUNOSI at the dose received in the stable-dose phase or switch to placebo. Compared to patients who remained on SUNOSI, patients randomized to placebo experienced statistically significant worsening of sleepiness as measured by the MWT and ESS (Table 8).

Study 4 was a 52-week, open-label study in 638 patients with either narcolepsy or OSA who had completed a prior trial. During a 2-week, open-label titration phase, patients were started on SUNOSI 75 mg once daily, and were titrated to the maximum tolerable dose between 75 mg and 300 mg per day (two times the maximum recommended daily dose). Patients remained on this dose during a subsequent open-label treatment period of either 38 (for patients previously enrolled in Study 1 or Study 2) or 50 (all others) weeks. A 2-week randomized-withdrawal period was incorporated into the study. After 6 months of stable-dose treatment, 282 patients (79 with narcolepsy; 203 with OSA) entered the randomized-withdrawal period. Patients were randomized 1:1 to either continue to receive SUNOSI at the dose received in the maintenance phase or to switch to placebo. The primary efficacy endpoint was change from the beginning to the end of the randomized-withdrawal period in ESS. Compared to patients who remained on SUNOSI, patients randomized to placebo experienced statistically significant worsening of sleepiness as measured by the ESS (Table 8).

Table 8: Efficacy Results from Randomized Withdrawal Studies in Patients with Narcolepsy and OSA in Studies 3 and 4
Indication/ Study | Endpoint | Treatment Groups (N) | Beginning of Randomized Withdrawal Period (Baseline) Mean (SD) | LS Mean Change from Baseline (SE) | Difference from Placebo (95% CI)
OSA STUDY 3 | MWT (minutes) | Placebo (62) | 29.0 (9.9) | -12.1 (1.3)
OSA STUDY 3 | MWT (minutes) | SUNOSI* (60) | 31.7 (9.2) | -1.0 (1.4) | 11.2 (7.8, 14.6)
OSA STUDY 3 | ESS Score | Placebo (62) | 5.9 (3.8) | 4.5 (0.7)
OSA STUDY 3 | ESS Score | SUNOSI* (60) | 6.4 (4.4) | -0.1 (0.7) | -4.6 (-6.4, -2.8)
OSA and Narcolepsy STUDY 4 | ESS Score | Placebo (141) | 7.8 (5.0) | 5.3 (0.4)
OSA and Narcolepsy STUDY 4 | ESS Score | SUNOSI* (139) | 7.3 (5.3) | 1.6 (0.4) | -3.7 (-4.8, -2.7)
SD = standard deviation; SE = standard error; LS Mean = least square mean; CI = confidence interval
For MWT, maximum possible score is 40 minutes; negative changes indicate worsening.
For ESS, scores range from 0 to 24; positive changes indicate worsening.
* Statistically significantly superior to placebo after adjusting for multiplicity.

16 HOW SUPPLIED / STORAGE AND HANDLING

STORAGE AND HANDLING

How Supplied

SUNOSI is packaged in 30-count white, high density polyethylene (HDPE) bottles.

SUNOSI tablets, 75 mg - dark yellow oblong tablet with "75" debossed on one side and a functional score line on the opposite side.
NDC 81968-350-01: Bottles of 30 with child-resistant closure

SUNOSI tablets, 150 mg - yellow oblong tablet with "150" debossed on one side.
NDC 81968-351-01: Bottles of 30 with child-resistant closure

Storage

Store SUNOSI at 20 to 25°C (68°to 77°F); excursions permitted between 15°to 30°C (59°to 86°F) (see USP controlled room temperature).

17 PATIENT COUNSELING INFORMATION

Advise the patient to read the FDA-approved patient labeling (Medication Guide).

Potential for Abuse and Dependence

Advise patients that SUNOSI is a federally controlled substance because it has the potential to be abused [see Drug Abuse and Dependence (9)]. Advise patients to keep their medication in a secure place and to dispose of unused SUNOSI as recommended in the Medication Guide.

Primary OSA Therapy Use

Inform patients that SUNOSI is not indicated to treat the airway obstruction in OSA and they should use a primary OSA therapy, such as CPAP, as prescribed to treat the underlying obstruction [see Indications and Usage (1)]. SUNOSI is not a substitute for primary OSA therapy.

Blood Pressure and Heart Rate Increases

Instruct patients that SUNOSI can cause elevations of their blood pressure and pulse rate and that they should be monitored for such effects [see Warnings and Precautions (5.1)].

Psychiatric Symptoms

Instruct patients to contact their healthcare provider if they experience, anxiety, insomnia, irritability, agitation, or signs of psychosis or bipolar disorders [see Warnings and Precautions (5.2)].

Lactation

Advise breastfeeding patients using SUNOSI to monitor infants for signs of agitation, insomnia, and reduced weight [see Use in Specific Populations (8.2)].

For more information, visit www.SUNOSI.com

Distributed by:
Axsome Therapeutics, Inc.
New York, NY 10007

For patent information: www.axsome.com/IP

© 2023 Axsome Therapeutics, Inc.

SUN-USPI-004.000-20230630

MEDICATION GUIDE

SUNOSI® (suh-NOH-see)
(solriamfetol)
tablets, for oral use, CIV

What is SUNOSI?

SUNOSI is a prescription medicine used to improve wakefulness in adults with excessive daytime sleepiness that is associated with narcolepsy or obstructive sleep apnea (OSA).

- It is not known if SUNOSI is safe and effective in children.
- SUNOSI is not for use to treat the underlying cause of airway obstruction in people with OSA. SUNOSI does not take the place of using your continuous positive airway pressure (CPAP) machine or other devices that your healthcare provider has prescribed for the treatment of OSA. It is important that you continue to use these treatments as prescribed by your healthcare provider.

SUNOSI is a federally controlled substance (CIV) because it contains solriamfetol that can be a target for people who abuse prescription medicines or street drugs. Keep SUNOSI in a safe place to protect it from theft. Never give your SUNOSI to anyone else, because it may cause death or harm them. Selling or giving away SUNOSI may harm others and is against the law. Tell your healthcare provider if you have ever abused or been dependent on alcohol, prescription medicines or street drugs.

Do not take SUNOSI if you are taking or have stopped taking within the past 14 days a medicine used to treat depression called a monoamine oxidase inhibitor (MAOI).

Before taking SUNOSI, tell your healthcare provider about all your medical conditions, including if you:

- have heart problems or have had a heart attack
- have had a stroke
- have high blood pressure
- have kidney problems or diabetes
- have high cholesterol in your blood
- have a history of mental health problems, including psychosis and bipolar disorders
- have a history of drug or alcohol abuse or addiction
- are pregnant or planning to become pregnant. It is not known if SUNOSI will harm your unborn baby.
  - Pregnancy Registry: There is a pregnancy registry for women who take SUNOSI during pregnancy. The purpose of this registry is to collect information about the health of you and your baby. Talk to your healthcare provider about how you can take part in this registry. For more information or to participate in the registry, call 1-877-283-6220 or go to www.SunosiPregnancyRegistry.com
- are breastfeeding or plan to breastfeed. SUNOSI passes into your breastmilk. Talk to your healthcare provider about the best way to feed your baby if you take SUNOSI.

Tell your healthcare provider about all the medicines you take, including prescription or over-the-counter medicines, vitamins, or herbal supplements.

SUNOSI and some other medicines may affect each other causing possible serious side effects. SUNOSI may affect the way other medicines work and other medicines may affect the way SUNOSI works.

Especially tell your healthcare provider if you take a medicine used to treat depression called a monoamine oxidase inhibitor (MAOI).

Know the medicines you take. Keep a list of them to show your healthcare provider and pharmacist when you get a new medicine.

How should I take SUNOSI?

- Take SUNOSI exactly as your healthcare provider tells you to. Do not change your dose of SUNOSI without talking to your healthcare provider.
- Your healthcare provider may need to change the dose of SUNOSI until it is the right dose for you.
- Take SUNOSI by mouth 1 time each day when you first wake up. Avoid taking SUNOSI within 9 hours of your planned bedtime. If you take SUNOSI too close to your bedtime, you may find it harder to go to sleep.
- SUNOSI can be taken with or without food.
- Depending on your prescribed dose, your healthcare provider may tell you to swallow your SUNOSI tablet whole or split the SUNOSI tablet in half at the score line in the middle of the tablet. Ask your healthcare provider if you have questions about how to split the SUNOSI tablet in half the right way.
- If you take too much SUNOSI, call your healthcare provider or go to the nearest hospital emergency room right away.

What are the possible side effects of SUNOSI?
SUNOSI may cause serious side effects, including:

- Increased blood pressure and heart rate. SUNOSI can cause blood pressure and heart rate increases that can increase the risk of heart attack, stroke, heart failure and death. Your healthcare provider should check your blood pressure before you start and during treatment with SUNOSI. Your healthcare provider may decrease your dose or tell you to stop taking SUNOSI if you develop high blood pressure that does not go away during treatment with SUNOSI.
- Mental (psychiatric) symptoms including anxiety, problems sleeping (insomnia), irritability and agitation. Tell your healthcare provider if you develop anxiety, problems sleeping, irritability, agitation. Your healthcare provider may change your dose or tell you to stop taking SUNOSI if you develop side effects during treatment with SUNOSI.

The most common side effects of SUNOSI include:

- headache
- decreased appetite
- problems sleeping
- nausea
- anxiety

These are not all the possible side effects of SUNOSI.

Call your doctor for medical advice about side effects. You may report side effects to FDA at 1-800-FDA-1088.

How should I store SUNOSI?

- Store SUNOSI at room temperature between 68°F to 77°F (20°C to 25°C).
- Store SUNOSI in a safe place, like a locked cabinet.
- Dispose of remaining, unused, or expired SUNOSI by a medication take-back program at authorized collection sites such as retail pharmacies, hospital or clinic pharmacies, and law enforcement locations. If no take-back program or authorized collector is available, mix SUNOSI with an undesirable, nontoxic substance such as dirt, cat litter, or used coffee grounds to make it less appealing to children and pets. Place the mixture in a container such as a sealed plastic bag and throw away SUNOSI in the household trash.

Keep SUNOSI and all medicines out of the reach of children.

General information about the safe and effective use of SUNOSI.
Medicines are sometimes prescribed for purposes other than those listed in a Medication Guide. Do not use SUNOSI for a condition for which it was not prescribed. Do not give SUNOSI to other people, even if they have the same symptoms that you have. It may harm them. You can ask your pharmacist or healthcare provider for information about SUNOSI that is written for health professionals.

What are the ingredients in SUNOSI?

Active Ingredient: solriamfetol

Inactive Ingredients: hydroxypropyl cellulose and magnesium stearate. In addition, the film coating contains: iron oxide yellow, polyethylene glycol, polyvinyl alcohol, titanium dioxide, and talc.

Distributed by: Axsome Therapeutics, Inc. New York, NY 10007
SUNOSI is a trademark of Axsome Therapeutics, Inc. or its affiliates.
For more information, go to www.SUNOSI.com or call 1-800-484-1672.

This Medication Guide has been approved by the U.S. Food and Drug Administration.

SUN-USMG-003.000-20230630

Revised: 06/2023